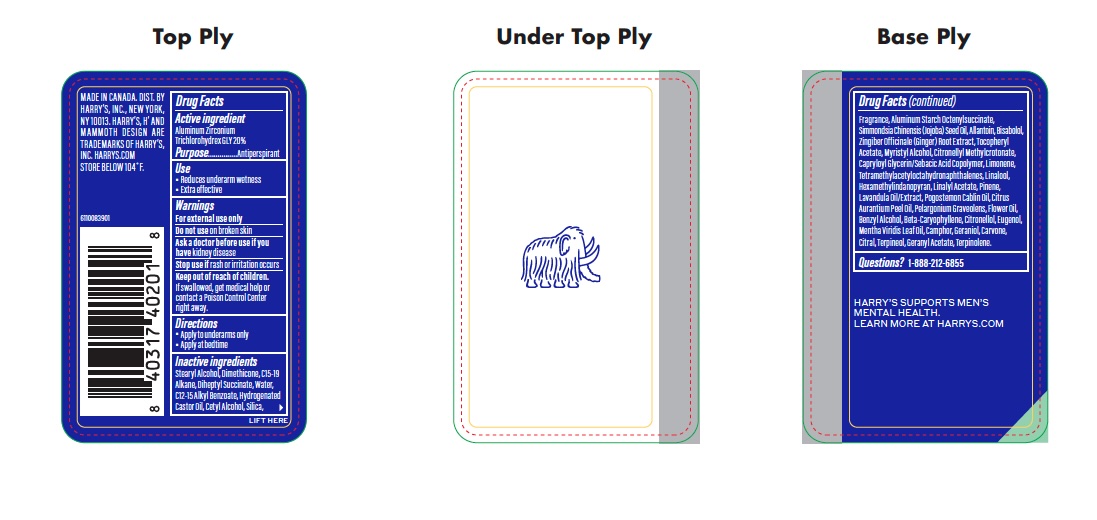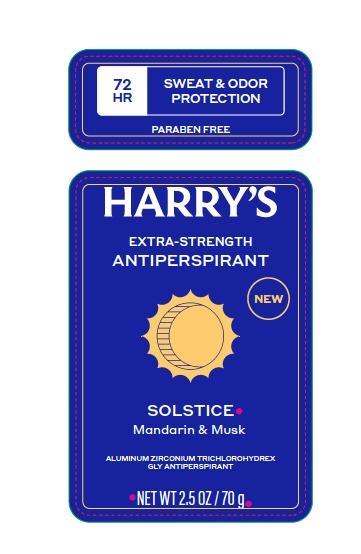 DRUG LABEL: Harrys Extra Strength Antiperspirant Solstice
NDC: 70533-017 | Form: STICK
Manufacturer: Harry's, Inc.
Category: otc | Type: HUMAN OTC DRUG LABEL
Date: 20251022

ACTIVE INGREDIENTS: ALUMINUM ZIRCONIUM TRICHLOROHYDREX GLY 200 mg/1 g
INACTIVE INGREDIENTS: .ALPHA.-BISABOLOL, (+/-)-; CITRUS AURANTIUM PEEL OIL; CITRONELLOL; CAMPHOR (NATURAL); CARVONE; ALLANTOIN; C12-15 ALKYL BENZOATE; LAVENDER OIL; ALPHA-TOCOPHEROL ACETATE; CAPRYLOYL GLYCERIN/SEBACIC ACID COPOLYMER (2000 MPA.S); LINALYL ACETATE; PINENE; POGOSTEMON CABLIN OIL; PELARGONIUM GRAVEOLENS FLOWER OIL; BETA-CARYOPHYLLENE; GERANYL ACETATE; DIMETHICONE; WATER; CETYL ALCOHOL; CITRAL; TERPINEOL; GINGER; ALUMINUM STARCH OCTENYLSUCCINATE; HEXAMETHYLINDANOPYRAN; MYRISTYL ALCOHOL; LIMONENE, (+/-)-; TERPINOLENE; FRAGRANCE 13576; DIHEPTYL SUCCINATE; SILICON DIOXIDE; CITRONELLYL METHYLCROTONATE; BENZYL ALCOHOL; STEARYL ALCOHOL; EUGENOL; GERANIOL; C15-19 ALKANE; HYDROGENATED CASTOR OIL; JOJOBA OIL; TETRAMETHYL ACETYLOCTAHYDRONAPHTHALENES; LINALOOL, (+/-)-; MENTHA VIRIDIS (SPEARMINT) LEAF OIL

Extra Strength AP - Solstice

ACTIVE INGREDIENT

Aluminum Zirconium Trichlorohydrex GLY 20%

PURPOSE

Antiperspirant

INDICATIONS AND USAGE

- Reduces underarm wetness
- Extra effective

WARNINGS

For external use only

Do not use on broken skin

Ask a doctor before use if you have kidney disease

Stop use if rash or irritation occurs

Keep out of reach of children. If swallowed, get medical help or contact a Poison Control Center right away.

Directions

- Apply to underarms only
- Apply at bedtime

Inactive ingredients

Stearyl Alcohol, Dimethicone, C15-19 Alkane, Diheptyl Succinate, Water, C12-15 Alkyl Benzoate, Hydrogenated Castor Oil, Cetyl Alcohol, Silica, Fragrance, Aluminum Starch Octenylsuccinate, Simmondsia Chinensis (Jojoba) Seed Oil, Allantoin, Bisabolol, Zingiber Officinale (Ginger) Root Extract, Tocopheryl Acetate, Myristyl Alcohol, Citronellyl Methylcrotonate, Capryloyl Glycerin/Sebacic Acid Copolymer, Limonene, Tetramethyl Acetyloctahydronaphthalenes, Linalool, Hexamethylindanopyran, Linalyl Acetate, Pinene, Lavandula Oil/Extract, Pogostemon Cablin Oil, Citrus Aurantium Peel Oil, Pelargonium Graveolens Flower Oil, Benzyl Alcohol, Beta-Caryophyllene, Citronellol, Eugenol, Mentha Viridis Leaf Oil, Camphor, Geraniol, Carvone, Citral, Terpineol, Geranyl Acetate, Terpinolene.

Questions? 1-888-212-6855